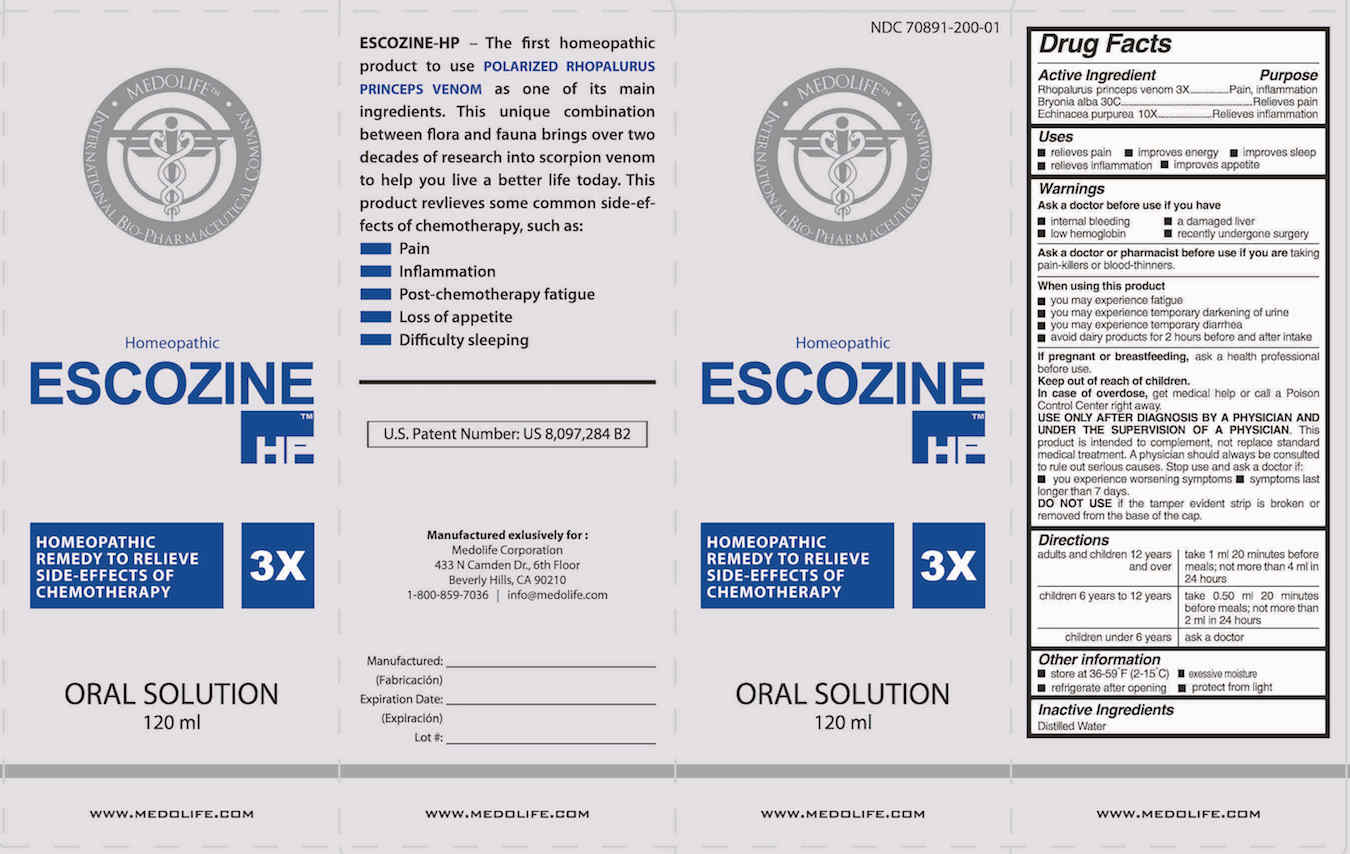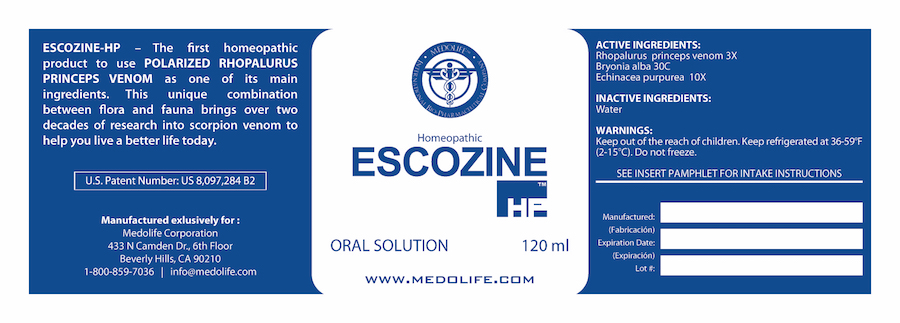 DRUG LABEL: Escozine HP
NDC: 70891-201 | Form: LIQUID
Manufacturer: Medolife Corporation
Category: homeopathic | Type: HUMAN OTC DRUG LABEL
Date: 20240125

ACTIVE INGREDIENTS: ECHINACEA PURPUREA 10 [hp_X]/1 mL; BRYONIA ALBA ROOT 30 [hp_C]/1 mL; RHOPALURUS PRINCEPS VENOM 3 [hp_X]/1 mL
INACTIVE INGREDIENTS: WATER

Escozine HP

ACTIVE INGREDIENTS:

Rhopalurus Princeps Venom 3X

Bryonia Alba 30C

Echinacea purpurea 10X

WARNINGS:

Do not use if the tamper evident strip is broken or removed from the base of the cap.

DIRECTIONS:

Adults and children 12 years and over: | Take 1 ml 20 minutes before meals; not more than 4 ml in 24 hours
Children 6 years to 12 years children: | Take 0.50 ml 20 minutes before meals ; not more than 2 ml in 24 hours
Under 6 years | Ask a doctor

INACTIVE INGREDIENTS:

Distilled water

KEEP OUT OF REACH OF CHILDREN: In case of overdose, get medical help or call a Poison Control Center right away.

INDICATIONS:

Uses

- relieves pain
- improves energy
- improves sleep
- relieves inflammation
- improves appetite

QUESTIONS:

Medolife Corporation
1-800-859-7036
info@medolife.com

PURPOSE:

Rhopalurus princeps venom 3x..Pain, inflammation
Bryonia alba 30C .............Relieves pain
Echinacea purpurea 10X........Relieves inflammation

If pregnant or breast feeding, ask a health professional before use.

ASK DOCTOR:

USE ONLY AFTER DIAGNOSIS BY A PHYSICIAN AND UNDER THE SUPERVISION OF A PHYSICIAN. This product is intended to complement not replace standard medical treatment. A physician should always be consulted to rule out serious causes.

Ask a doctor before use if you have

- internal bleeding
- low hemoglobin
- a damaged liver
- recently undergone surgery

OTHER INFORMATION:

- store at 36-59°F (2-15°C)
- refrigerate after opening
- protect from excessive moisture
- protect from light

When using this product:

- you may experience fatigue
- you may experience temporary darkening of urine
- you may experience temporary diarrhea
- avoid dairy products for 2 hours before and after intake

Ask a doctor or pharmacist before use if you are taking pain-killers or blood-thinners.

Stop use and ask doctor if

- you experience worsening symptoms
- symptoms last longer than 7 days.

PACKAGE LABEL DISPLAY:

Principal display panel